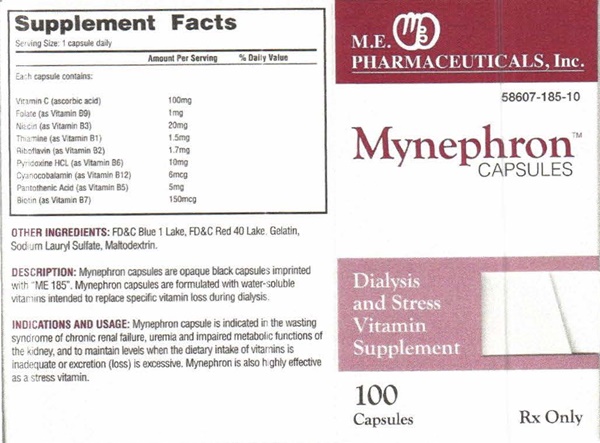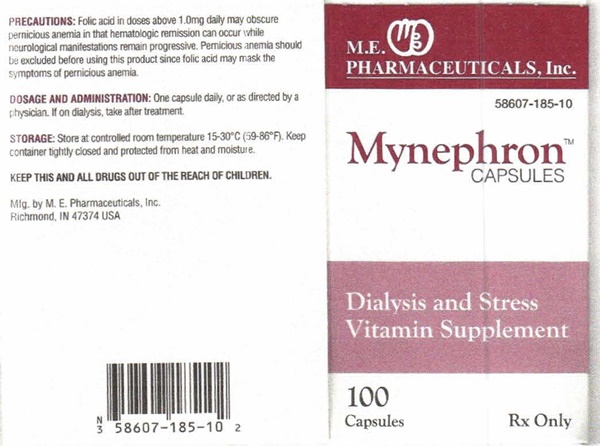 DRUG LABEL: Myhephron
NDC: 58607-185 | Form: CAPSULE
Manufacturer: Martin Ekwealor Pharmaceu
Category: prescription | Type: HUMAN PRESCRIPTION DRUG LABEL
Date: 20160802

ACTIVE INGREDIENTS: ASCORBIC ACID 100 mg/1 1; FOLIC ACID 1 mg/1 1; NIACIN 20 mg/1 1; THIAMINE 1.5 mg/1 1; RIBOFLAVIN 1.7 mg/1 1; PYRIDOXINE 10 mg/1 1; CYANOCOBALAMIN 6 ug/1 1; PANTOTHENIC ACID 5 mg/1 1; BIOTIN 150 ug/1 1
INACTIVE INGREDIENTS: FD&C BLUE NO. 1; FD&C RED NO. 40; GELATIN; SODIUM LAURETH-3 SULFATE; MALTODEXTRIN

Mynephron - 185

Supplemental Facts Serving Size: 1 capsule daily

Each capsule contains:

Amount Per Serving

Vitamin C (ascorbic acid) 100 mg

Folate (as Vitamin B9) 1 mg

Niacin (as Vitamin B3) 20 mg

Thiamine (as Vitamin B1) 1.5 mg

Riboflavin (as Vitamin B2) 1.7 mg

Pyridoxine HCL (as Vitamin B6) 10 mg

Cyanocobalamin (as Vitamin B12) 6 mcg

Pantothenic Acid (as Vitamin B5) 5 mg

Biotin (as Vitamin B7) 150 mcg

DESCRIPTION:

Mynephron capsules are opaque black capsules imprinted with "ME 185". Mynephron capsules are formulated with water-soluble vitamins intended to replace specific vitamin loss during dialysis.

INDICATIONS AND USAGE:

Mynephron capsule is indicated in the wasting syndrome of chronic renal failure, uremia and impaired metabolic functions of the kidney, and to maintain levels when the dietary intake of vitamins is inadequate or excretion (loss) is excessive. Mynephron is also highly effective as a stress vitamin.

OTHER INGREDIENTS:

FD&C Blue 1 Lake, FD&C Red 40 Lake, Gelatin, Sodium Lauryl Sulfate, Maltodextrin.

PRECAUTIONS:

Folic acid in doses above 1.0 mg daily may obscure pernicious anemia in that hematologic remission can occur while neurological manifestions remain progressive. Pernicious anemia should be excluded before using this product since folic acid may mask the symptoms of pernicious anemia.

DOSAGE AND ADMINISTRATION:

One capsule daily, or as directed by a physician. If on dialysis, take after treatment.

STORAGE:

Store at room temperature 15-30°C (59-86°F). Keep container tightly closed and protected from heat and moisture.

KEEP THIS AND ALL DRUGS OUT OF THE REACH OF CHILDREN.

Mynephron product label

M.E.

PHARMACEUTICALS, INC.

58607-185-10

Mynephron™

CAPSULES

Dialysis and Stress Vitamin Supplement

100 Capsules

Rx Only

M.E. Pharmaeuticals, Inc.

Richmond, IN 47374 USA